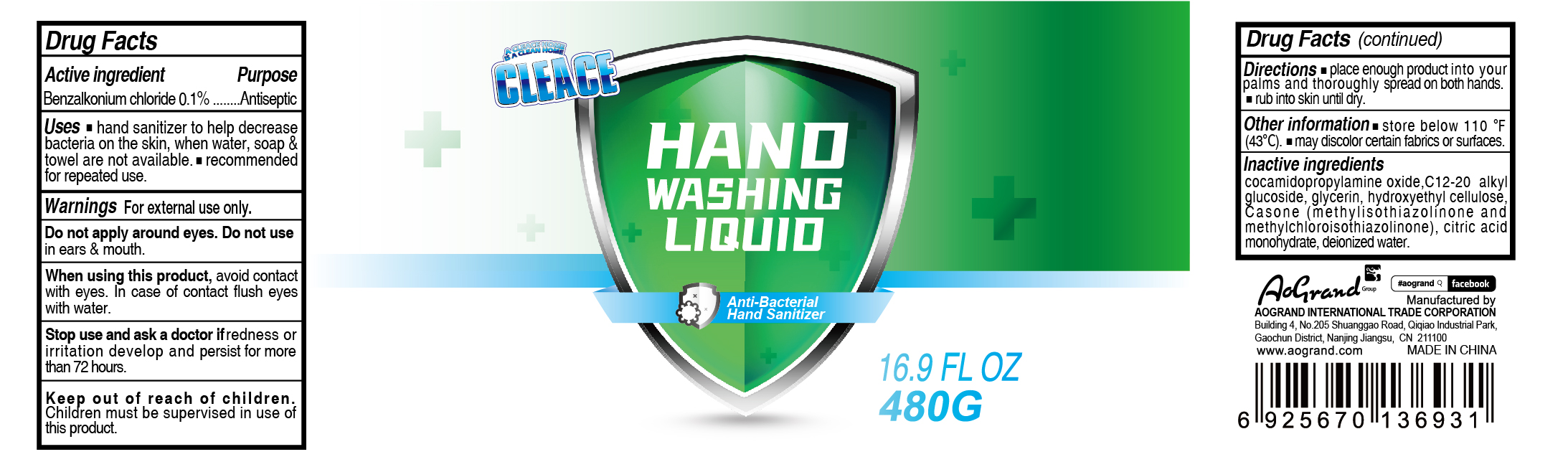 DRUG LABEL: Antibacterial Hand Sanitizer
NDC: 74621-006 | Form: GEL
Manufacturer: Aogrand International Trade Corporation
Category: otc | Type: HUMAN OTC DRUG LABEL
Date: 20230211

ACTIVE INGREDIENTS: BENZALKONIUM CHLORIDE 0.1 g/100 g
INACTIVE INGREDIENTS: ANHYDROUS CITRIC ACID; HYDROXYETHYL CELLULOSE (4000 MPA.S AT 1%); GLYCERIN; COCAMIDOPROPYLAMINE OXIDE; WATER; C12-20 ALKYL GLUCOSIDE; METHYLCHLOROISOTHIAZOLINONE/METHYLISOTHIAZOLINONE MIXTURE

Antibacterial Hand Sanitizer

Active Ingredient(s)

Benzalkonium Chloride 0.1%. Purpose: Antiseptic

Purpose

Antiseptic, Hand Sanitizer

Use

- hand Sannitizer to help decrease bacteria on the skin, when water, soap & towel are not available.
- recommended for repeated use

Warnings

For external use only.

DO NOT USE

Do not apply around eyes. Do not use in ears & mouth.

When using this product

avoid contact with eyes. In case of contact, flush eyes with water.

Stop use and ask a doctor

if redness or irritation develop and persist for more than 72 hours.

Keep out of reach of children. Children must be supervised in use of this product.

Directions

- Place enough product into your palms and thoroughly spread on both hands
- rub into skin until dry

Inactive ingredients

Cocamidopropylamine oxide, C12-20 Alkyl glycoside, glycerin, hydroxyethyl cellulose, Casone (methylisothiazolinone and methylchloroisothiazolinone), citric acid, deionized water

Other information

- store below 110F (43C)
- may discolor certain fabrics or surfaces

Package Label - Principal Display Panel

480g NDC: 74621-006-02